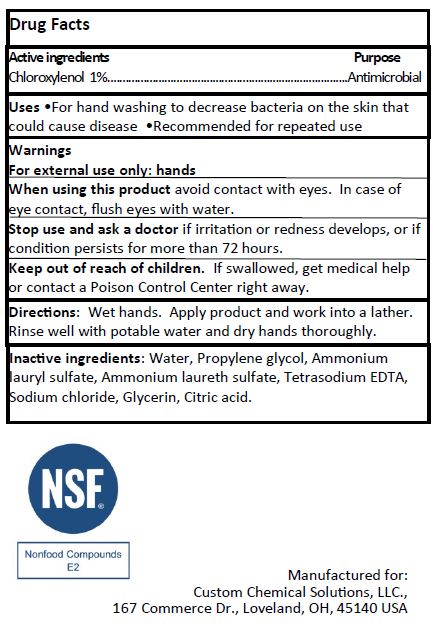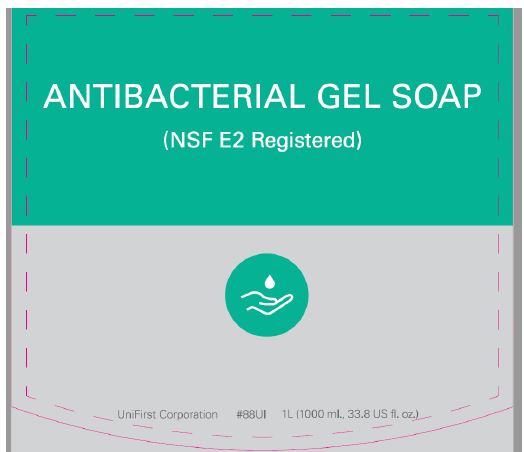 DRUG LABEL: Antibacterial
NDC: 77955-004 | Form: GEL
Manufacturer: Custom Chemical Solutions
Category: otc | Type: HUMAN OTC DRUG LABEL
Date: 20260113

ACTIVE INGREDIENTS: CHLOROXYLENOL 0.01 mg/1 mL
INACTIVE INGREDIENTS: WATER; PROPYLENE GLYCOL; AMMONIUM LAURETH-3 SULFATE; SODIUM CHLORIDE; GLYCERIN; CITRIC ACID MONOHYDRATE; AMMONIUM LAURYL SULFATE; EDETATE SODIUM

77955-004

Active ingredients

Chloroxylenol 1%

Purpose

Antimicrobial

Uses

- For handwashing to decrease bacteria on the skin that could cause disease
- Recommended for repeated use

Warnings

For external use only: hands

When using this productavoid contact with eyes.

In case of contact, flush eyes with water.

Stop use and ask a doctorif irritation or redness develops, or if condition persists for more than 72 hours.

Keep out of reach of children.

If swallowed, get medical help or contact a Poison Control Center right away.

Directions:

Wet hands

Apply product and work into a lather.

Rinse well with potable water and dry hands thoroughly.

Inactive ingredients:

Water, Propylene glycol, Ammonium Lauryl sulfate, Ammonium laureth sulfate, Tetrasodium EDTA, Sodium chloride, Glycerin, Citric acid.

PACKAGE LABEL

ANTIBACTERIAL GEL SOAP

(NSF E2 Registered)

UniFirst Corporation #88UI 1L(1000ml., 33.8 US fl. oz)